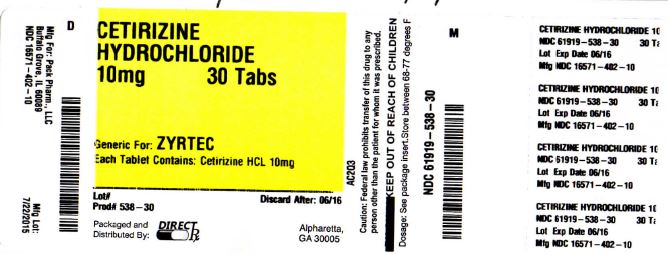 DRUG LABEL: Cetirizine Hydrochloride
NDC: 61919-538 | Form: TABLET
Manufacturer: DIRECT RX
Category: otc | Type: HUMAN OTC DRUG LABEL
Date: 20151109

ACTIVE INGREDIENTS: CETIRIZINE HYDROCHLORIDE 10 mg/1 1
INACTIVE INGREDIENTS: hypromelloses; lactose; magnesium stearate; starch, corn; POLYETHYLENE GLYCOLS; povidone; titanium dioxide

Cetirizine Hydrochloride

OTC - ACTIVE INGREDIENT SECTION

Active Ingredients (in each tablet) Purpose

Cetirizine HCl 10 mg..............................................................................................Antihistimine

OTC - PURPOSE SECTION

Temporarily relieves these symptoms due to hay fever or other upper respiratory allergies

- runny nose
- sneezing
- itchy, watery eyes
- itching of the nose or throat

WARNINGS SECTION

Do Not Use if you have ever had an allergic reaction to this product or any of its ingredients or to an antihistamine containing hydroxyzine.

OTC - ASK DOCTOR SECTION

Ask a doctor before use if you have liver or kidney disease. Your doctor should determine if you need a different dose.

OTC - ASK DOCTOR/PHARMACIST SECTION

Ask a doctor or pharmacist before use if you are taking tranquilizers or sedatives.

OTC - WHEN USING SECTION

- drowsines may occur
- avoid alcoholic drinks
- alcohol, sedatives, and tranquilizers may increase drowsiness
- be careful when driving a motor vehicle or operating machinary

INDICATIONS & USAGE SECTION

drowsines may occur
avoid alcoholic drinks
alcohol, sedatives, and tranquilizers may increase drowsiness
be careful when driving a motor vehicle or operating machinary.

OTC - STOP USE SECTION

Stop use and ask a doctor if an allergic reaction to this product occurs. Seek medical help right away.

OTC - PREGNANCY OR BREAST FEEDING SECTION

- if breast-feeding: not recommended
- if pregnant: ask a health professional before use.

OTC - KEEP OUT OF REACH OF CHILDREN SECTION

In case of overdose, get medical help or contact Poison Control Center right away.

INSTRUCTIONS FOR USE SECTION

Adults and children 6 years and over | one 10 mg tablet once daily, do not take more than one 10 mg tablet in 24 hours. A 5 mg product may be appropriate for less sever symptoms.
Adults 65 years and over | Ask a doctor
Children under 6 years of age | Ask a doctor
Consumers with liver or kidney disease | Ask a doctor

DOSAGE & ADMINISTRATION SECTION

Adults and children 6
years and over
one 10 mg tablet once daily, do not take more than one 10 mg tablet in 24 hours. A 5 mg product may be appropriate for less sever symptoms.

Adults 65 years and over
Ask a doctor

Children under 6 years of age
Ask a doctor

Consumers with liver or kidney disease
Ask a doctor

OTHER SAFETY INFORMATION

store between 20° to 25°C (68° to 77°F)

INACTIVE INGREDIENT SECTION

Hypromellose, lactose, magnesium stearate, maize starch, polyethylene glycol, povidone, titanium dioxide.

OTC - QUESTIONS SECTION

Call 1-866-562-4597

SPL UNCLASSIFIED SECTION

Manufactured for PACK Pharmaceuticals, LLC

Buffalo Grove, IL 60089, USA

Manufactured by Unique Pharmaceutical Laboratories (A Div. of J. B. Chemicals & Pharmaceuticals Ltd.),

Mumbai 400 030, India